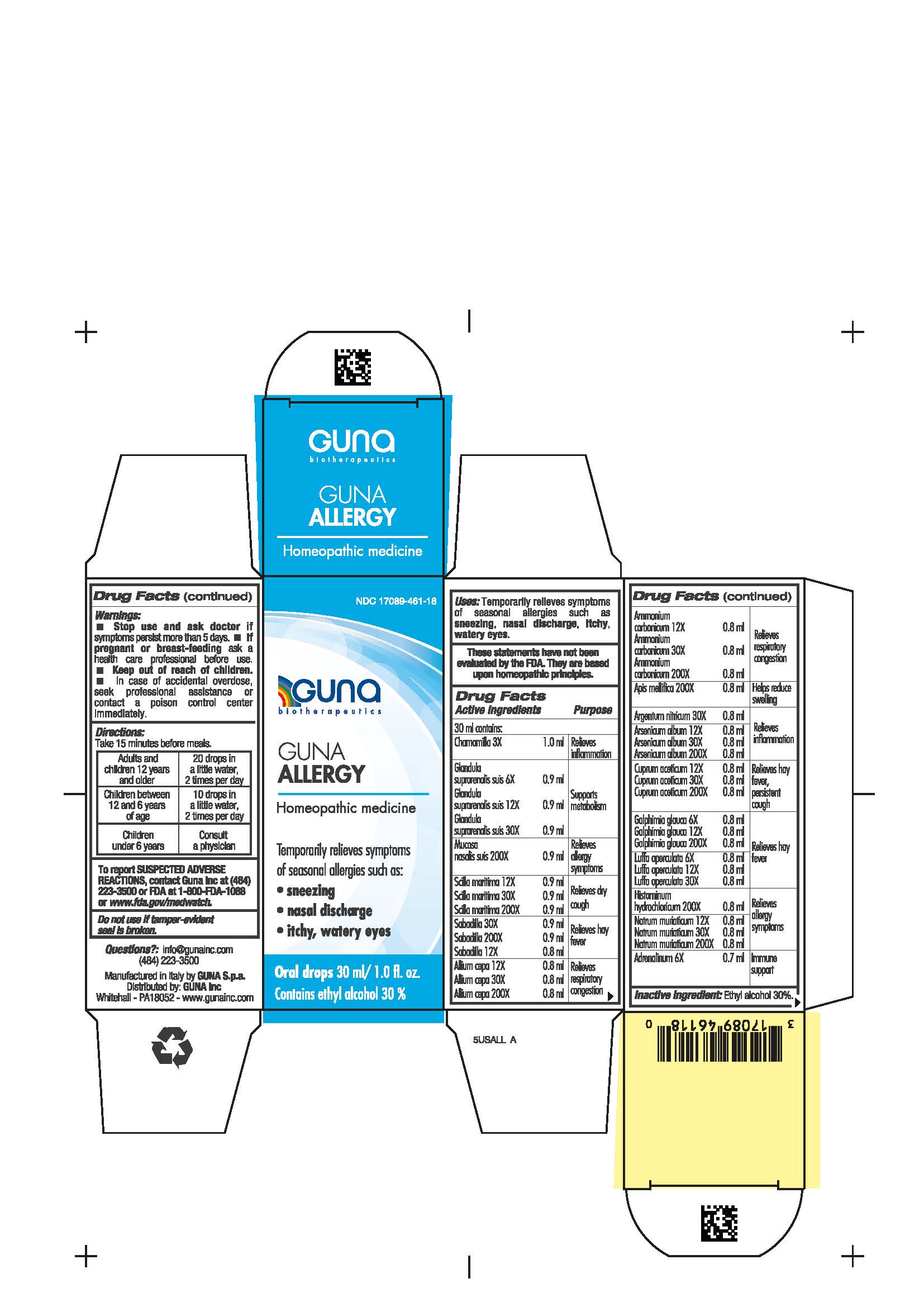 DRUG LABEL: GUNA ALLERGY
NDC: 17089-461 | Form: SOLUTION/ DROPS
Manufacturer: Guna spa
Category: homeopathic | Type: HUMAN OTC DRUG LABEL
Date: 20201023

ACTIVE INGREDIENTS: HISTAMINE DIHYDROCHLORIDE 200 [hp_X]/30 mL; SUS SCROFA ADRENAL GLAND 6 [hp_X]/30 mL; EPINEPHRINE 6 [hp_X]/30 mL; APIS MELLIFERA 200 [hp_X]/30 mL; CUPRIC ACETATE 12 [hp_X]/30 mL; SILVER NITRATE 30 [hp_X]/30 mL; DRIMIA MARITIMA BULB 12 [hp_X]/30 mL; GALPHIMIA GLAUCA FLOWERING TOP 6 [hp_X]/30 mL; SCHOENOCAULON OFFICINALE SEED 12 [hp_X]/30 mL; SODIUM CHLORIDE 12 [hp_X]/30 mL; LUFFA OPERCULATA FRUIT 6 [hp_X]/30 mL; MATRICARIA CHAMOMILLA WHOLE 3 [hp_X]/30 mL; AMMONIUM CARBONATE 12 [hp_X]/30 mL; ONION 12 [hp_X]/30 mL; ARSENIC TRIOXIDE 12 [hp_X]/30 mL; SUS SCROFA NASAL MUCOSA 200 [hp_X]/30 mL
INACTIVE INGREDIENTS: ALCOHOL 9 mL/30 mL

GUNA ALLERGY

ACTIVE INGREDIENTS/PURPOSE

CHAMOMILLA 3X RELIEVES INFLAMMATION

GLANDULA SUPRARENALIS SUIS 6X 12X 30X SUPPORTS METABOLISM

MUCOSA NASALIS SUIS 200X RELIEVES ALLERGY SYMPTOMS

SCILLA MARITIMA 12X 30X 200X RELIEVES DRY COUGH

SABADILLA 12X 30X 200X RELIEVES HAY FEVER

ALLIUM CEPA 12X 30X 200X RELIEVES RESPIRATORY CONGESTION

AMMONIUM CARBONICUM 12X 30X 200X RELIEVES RESPIRATORY CONGESTION
APIS MELLIFICA 200X HELPS REDUCE SWELLING
ARGENTUM NITRICUM 30X RELIEVES INFLAMMATION

ARSENICUM ALBUM 12X 30X 200X RELIEVES INFLAMMATION
CUPRUM ACETICUM 12X 30X 200X RELIEVES HAY FEVER, PERSISTENT COUGH
GALPHIMIA GLAUCA 6X 12X 200X RELIEVES HAY FEVER
LUFFA OPERCULATA 6X 12X 30X RELIEVES HAY FEVER

HISTAMINUM HYDROCHLORICUM 200X RELIEVES ALLERGY SYMPTOMS
NATRUM MURIATICUM 12X 30X 200X RELIEVES ALLERGY SYMPTOMS

ADRENALINUM 6X IMMUNE SUPPORT

WARNINGS

- Stop use and ask doctor if symptoms persist more than 5 days.
- If pregnant or breast-feeding ask a health care professional before use.
- Keep out of reach of children.
- In case of accidental overdose, seek professional assistance or contact a poison control center immediately.
- Contains ethyl alcohol 30%

WARNINGS

Keep out of the reach of children

DIRECTIONS

Take 15 minutes before meals.

Adults and children 12 years and older: 20 drops in a little water 2 times per day
Children between 12 years and 6 years of age :10 drops in a little water 2 times per day
Children under 6 years: consult a physician

QUESTIONS

Questions?: info@gunainc.com, tel. (484) 223-3500

INDICATIONS AND USAGE

Take 15 minutes before meals.

Inactive ingredient: Ethyl alcohol 30%.

PURPOSE

TEMPORARILY RELIEVES SYMPTOMS OF SEASONAL ALLERGIES SUCH AS:

- SNEEZING
- NASAL DISCHARGE
- ITCHY, WATERY EYES

DO NOT USE

If tamper-evident seal is broken

stop use and ask doctor if symptoms persist more than 5 days